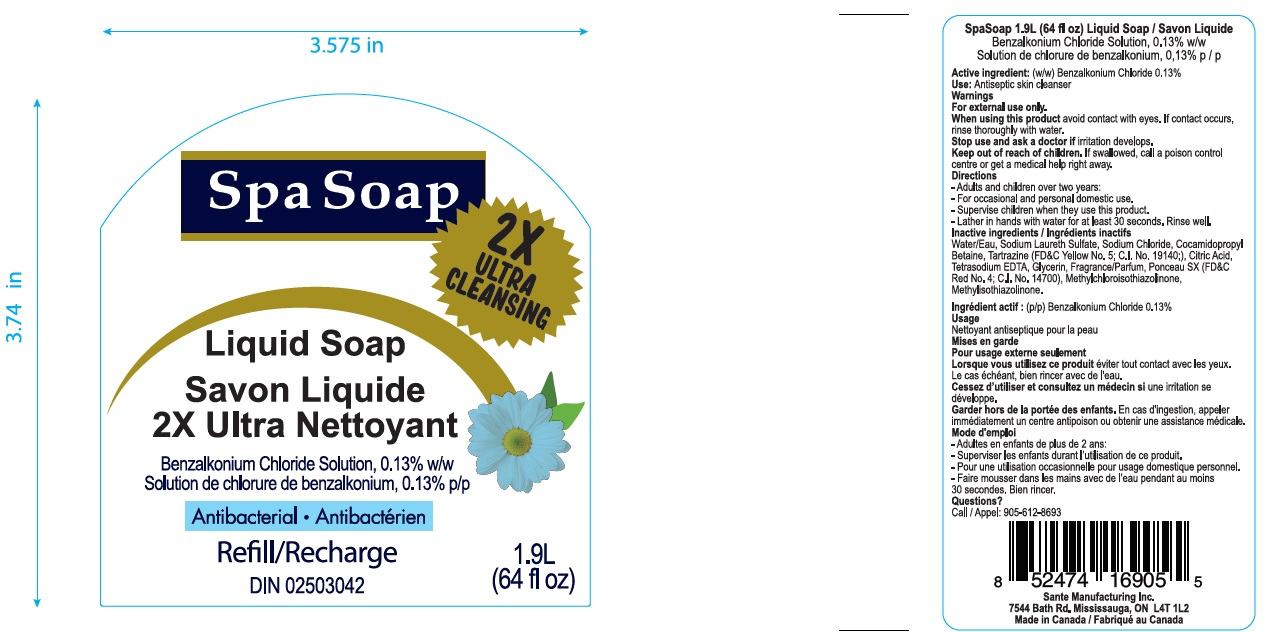 DRUG LABEL: Antibacterial
NDC: 71020-020 | Form: LIQUID
Manufacturer: Sante Manufacturing Inc
Category: otc | Type: HUMAN OTC DRUG LABEL
Date: 20250109

ACTIVE INGREDIENTS: BENZALKONIUM CHLORIDE 1.3 mg/1 mL
INACTIVE INGREDIENTS: CITRIC ACID MONOHYDRATE; WATER; SODIUM LAURETH SULFATE; COCAMIDOPROPYL BETAINE; SODIUM CHLORIDE; GLYCERIN; DITETRACYCLINE TETRASODIUM EDETATE; METHYLCHLOROISOTHIAZOLINONE; METHYLISOTHIAZOLINONE; FD&C YELLOW NO. 5; FD&C RED NO. 4

Spa Soap 2X Ultra cleansing

ACTIVE INGREDIENT

Benzalkonium Chloride - 0.13%

Purpose: Antiseptic skin cleanser

INDICATIONS AND USAGE

Uses for handwashing or decrease bacteria to the skin

DOSAGE AND ADMINISTRATION

Direction

- Adults and children over two years: For occasional and personal domestic use
- Supervise children when they use this product
- Lather in hands with water for at least 30 seconds. Rinse well

WARNINGS

For external use only

Stop use and ask a doctor if irritation or redness develops

When using this product

- do not get it into eyes. If contact occurs, rinse eye thoroughly with water

Keep out of reach of children

If swallowed, get medical help or contact a Poison Control Center right away

INACTIVE INGREDIENT

Water, Sodium Laureth Sulfate, Cocamidopropyl Betaine, Sodium Chloride, Citric Acid, Glycerin, Fragrance, Tetrasodium EDTA, Methylchloroisothiazolinone, Methylisothiazolinone, Yellow# 5 (Cl 19140), Red# 4 (Cl 14700)